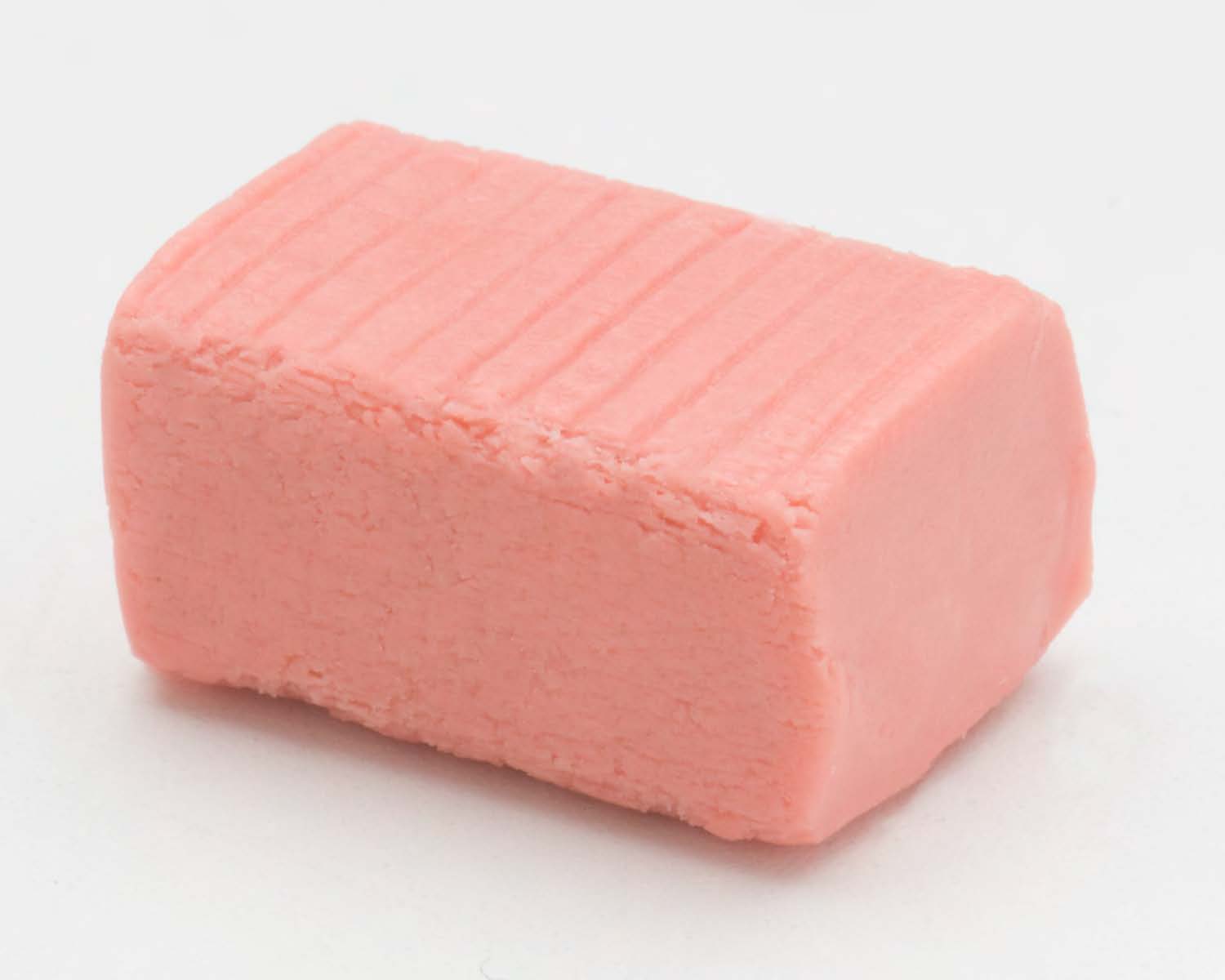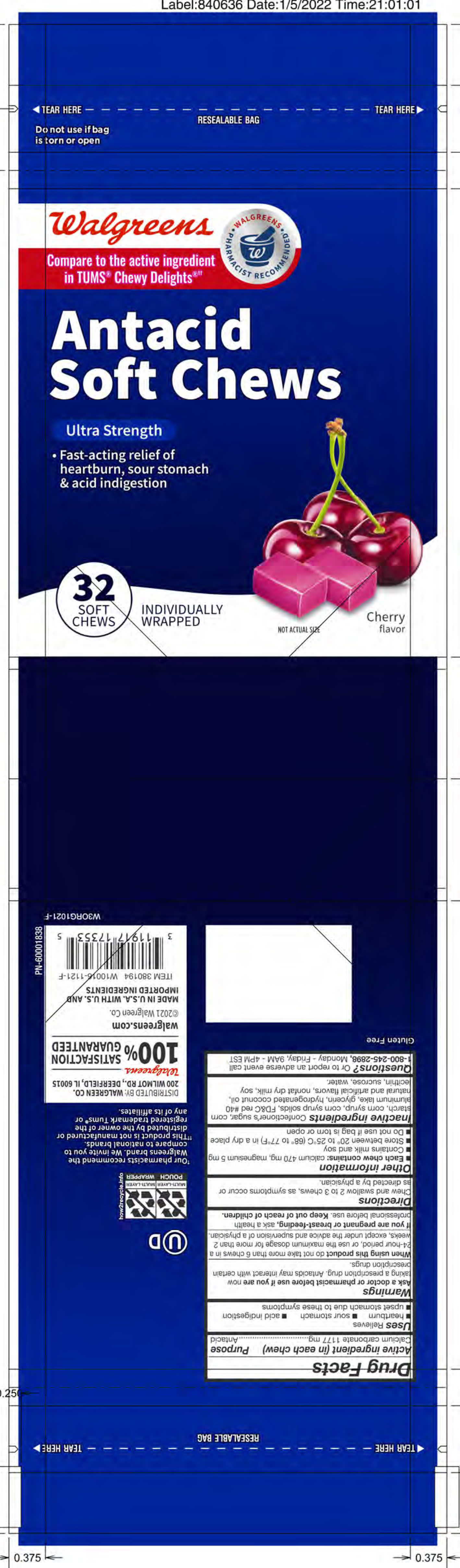 DRUG LABEL: Antacid Soft Chew
NDC: 0363-1081 | Form: TABLET, CHEWABLE
Manufacturer: Walgreen Co.
Category: otc | Type: HUMAN OTC DRUG LABEL
Date: 20251221

ACTIVE INGREDIENTS: CALCIUM CARBONATE 1177 mg/1 1
INACTIVE INGREDIENTS: SUCROSE

Calcium Carbonate 1177 mg

Active ingredient (in each chew)

Calcium carbonate 1177 mg

Purpose

Antacid

INDICATIONS AND USAGE

Uses: Relieves

- heartburn
- sour stomach
- acid indigestion
- upset stomach associated with these symptoms

Warnings

Ask a doctor or pharmacist before use if you are now taking a prescription drug. Antacids may interact with certain perscription drugs.

When using this product do not take more than 6 chews in a 24-hour period, or use the maximum dosage for more than 2 weeks, except under the advice and supervision of a physician.

PREGNANCY OR BREAST FEEDING

If you are pregnant or breast-feeding, ask a health professional before use.

Keep out of reach of children.

Directions

Chew and swallow 2 to 3 chews, as symptoms occur or as directed by a physician.

Other information

Each chew contains: calcium 470 mg, magnesium 5 mg

Contains milk and soy

Store between 20º to 25ºC (68º to 77ºF) in a dry place

INACTIVE INGREDIENT

Inactive ingredients: Corn starch, corn syrup, corn syrup solids, FD&C red #40 aluminum lake, glycerin, hydrogenated coconut oil, medium chain triglycerides, natural and artificail flavors, non-fat dried milk, soybean oil, soy lecithin and sucrose.

QUESTIONS

Questions? Or to report an adverse event call 1-800-245-2898, Monday - Friday, 9AM - 4PM EST